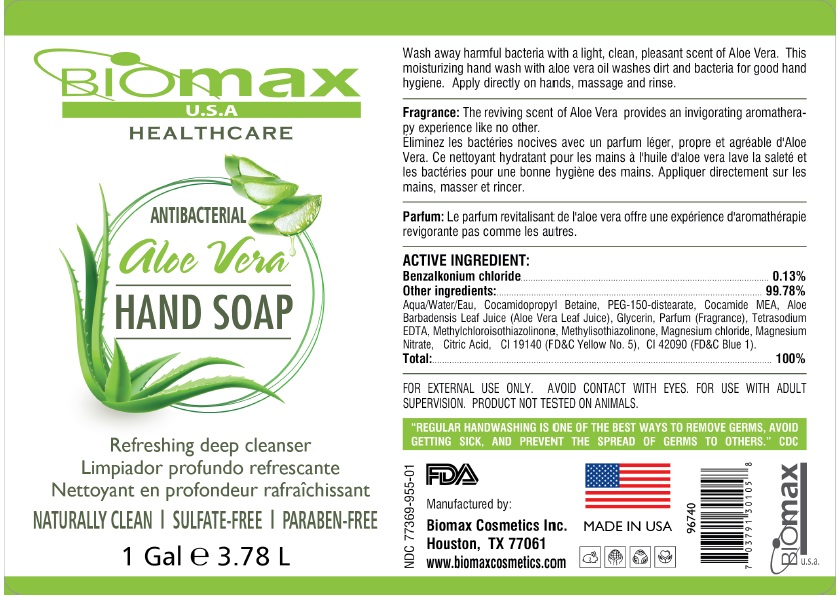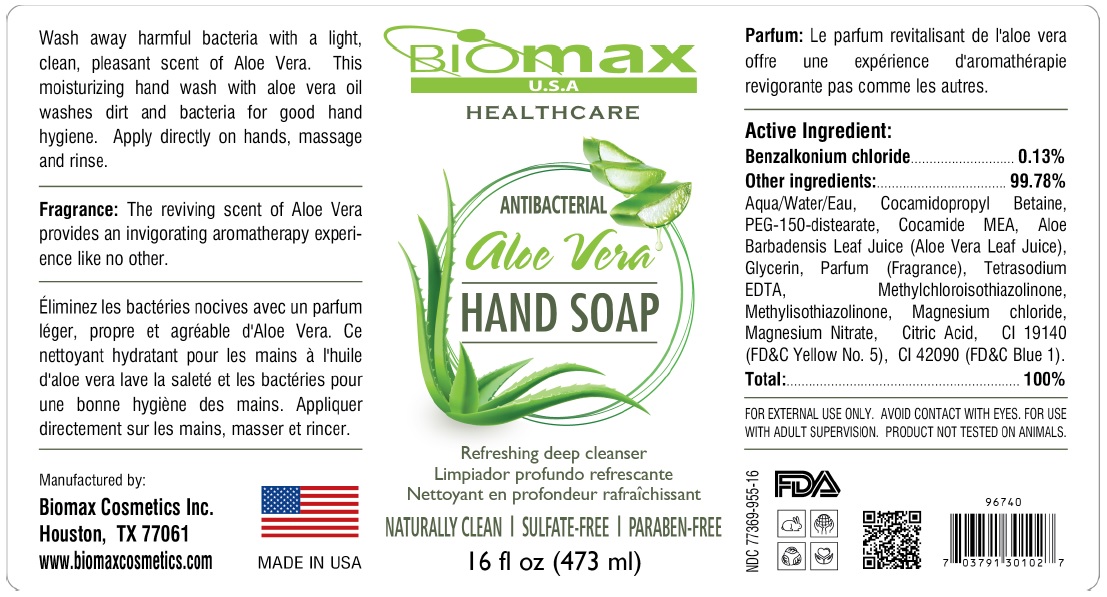 DRUG LABEL: Biomax USA ANTIBACTERIAL HAND WASH
NDC: 77369-955 | Form: SOAP
Manufacturer: Biomax Cosmetics
Category: otc | Type: HUMAN OTC DRUG LABEL
Date: 20200801

ACTIVE INGREDIENTS: BENZALKONIUM CHLORIDE 0.13 g/100 mL
INACTIVE INGREDIENTS: WATER; COCAMIDOPROPYL BETAINE; PEG-150 DISTEARATE; COCO MONOETHANOLAMIDE; ALOE VERA LEAF; GLYCERIN; EDETATE SODIUM; METHYLCHLOROISOTHIAZOLINONE; METHYLISOTHIAZOLINONE; MAGNESIUM CHLORIDE; MAGNESIUM NITRATE; CITRIC ACID MONOHYDRATE; FD&C YELLOW NO. 5; FD&C BLUE NO. 1

Biomax ANTIBACTERIAL aloe Vera HAND SOAP

Active ingredient:

Benzalkonium chloride..........0.13%

Purpose

Antibacterial

Other ingredients:..............99.78%

Aqua/Water/Eau, Cocamidopropyl Betaine, PEG-150-distearate, Cocamide MEA, Aloe Barbadensis Leaf Juice (Aloe Vera Leaf Juice), Glycerin, Parfum (Fragrance), Tetrasodium EDTA, Methylchloroisothiazolinone, Methylisothiazolinone, Magnesium chloride, Magnesium Nitrate, Citric Acid, CI 19140 (FD&C Yellow No. 5), CI 42090 (FD&C Blue 1).

Uses

• hand sanitizer to decrease bacteria on the skin
• recommended for repeated use

Warnings

FOR EXTERNAL USE ONLY. AVOID CONTACT WITH EYES. FOR USE WITH ADULT SUPERVISION. PRODUCT NOT TESTED ON ANIMALS.

Keep out of reach of children. If swallowed, get medical help or contact a Poison Control Center right away.

Directions

Apply directly on hands, massage and rinse.

HEALTHCARE

aloe vera

Refreshing deep cleanser

NATURALLY CLEAN | SULFATE-FREE | PARABEN-FREE

Wash away harmful bacteria with a light, clean, pleasant scent of Aloe Vera . This moisturizing hand wash with aloe vera oil washes dirt and bacteria for good hand hygiene.

Fragrance: The reviving scent of Aloe Vera provides an invigorating aromatherapy experience like no other.

Manufactured by:

Biomax Cosmetics Inc.

Houston, TX 77061

www.biomaxcosmetics.com

MADE IN USA